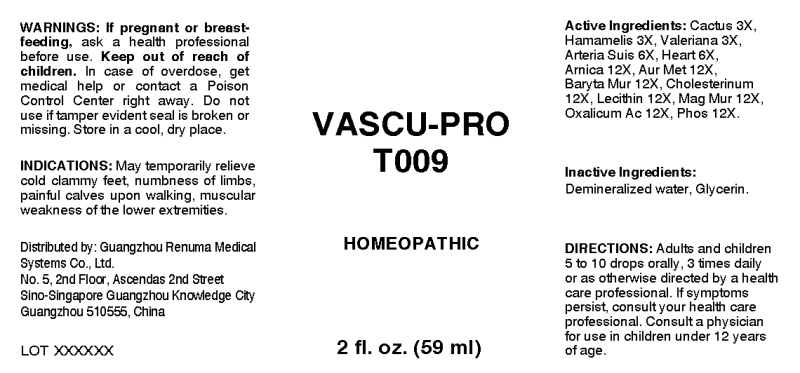 DRUG LABEL: Vascu-Pro
NDC: 71742-0003 | Form: LIQUID
Manufacturer: Guangzhou Renuma Medical Systems Co., Ltd
Category: homeopathic | Type: HUMAN OTC DRUG LABEL
Date: 20240123

ACTIVE INGREDIENTS: SELENICEREUS GRANDIFLORUS STEM 3 [hp_X]/1 mL; HAMAMELIS VIRGINIANA ROOT BARK/STEM BARK 3 [hp_X]/1 mL; VALERIAN 3 [hp_X]/1 mL; SUS SCROFA ARTERY 6 [hp_X]/1 mL; PORK HEART 6 [hp_X]/1 mL; ARNICA MONTANA WHOLE 12 [hp_X]/1 mL; GOLD 12 [hp_X]/1 mL; BARIUM CHLORIDE DIHYDRATE 12 [hp_X]/1 mL; CHOLESTEROL 12 [hp_X]/1 mL; LECITHIN, SOYBEAN 12 [hp_X]/1 mL; MAGNESIUM CHLORIDE 12 [hp_X]/1 mL; OXALIC ACID 12 [hp_X]/1 mL; PHOSPHORUS 12 [hp_X]/1 mL
INACTIVE INGREDIENTS: WATER; GLYCERIN

DRUG FACTS:

ACTIVE INGREDIENTS:

Cactus Grandiflorus 3X, Hamamelis Virginiana 3X, Valeriana Officinalis 3X, Arteria Suis 6X, Heart (Suis) 6X, Arnica Montana 12X, Aurum Metallicum 12X, Baryta Muriatica 12X, Cholesterinum 12X, Lecithin 12X, Magnesia Muriatica 12X, Oxalicum Acidum 12X, Phosphorus 12X.

INDICATIONS:

May temporarily relieve cold clammy feet, numbness of limbs, painful calves upon walking, muscular weakness of the lower extremities.

WARNINGS:

If pregnant or breast-feeding, ask a health care professional before use.
Keep out of reach of children. In case of overdose, get medical help or contact a Poison Control Center right away.
Do not use if tamper evident seal is broken or missing.
Store in cool, dry place.

KEEP OUT OF REACH OF CHILDREN:

In case of overdose, get medical help or contact a Poison Control Center right away.

DIRECTIONS:

Adults and children 5 to 10 drops orally, 1 to 2 times daily or as otherwise directed by a health care professional. If symptoms persist, consult your health care professional. Consult a physician for use in children under 12 years of age.

INDICATIONS:

May temporarily relieve cold clammy feet, numbness of limbs, painful calves upon walking, muscular weakness of the lower extremities.

INACTIVE INGREDIENTS:

Demineralized water, Glycerin

QUESTIONS:

Distributed by:
Guangzhou Renuma Medical
Systems Co., Ltd.
No. 5, 2nd Floor, Ascendas 2nd Street
Sino-Singapore Guangzhou Knowledge City
Guangzhou 510555, China

PACKAGE LABEL DISPLAY:

VASCU-PRO
T009
HOMEOPATHIC
2 fl. oz. (59 ml)